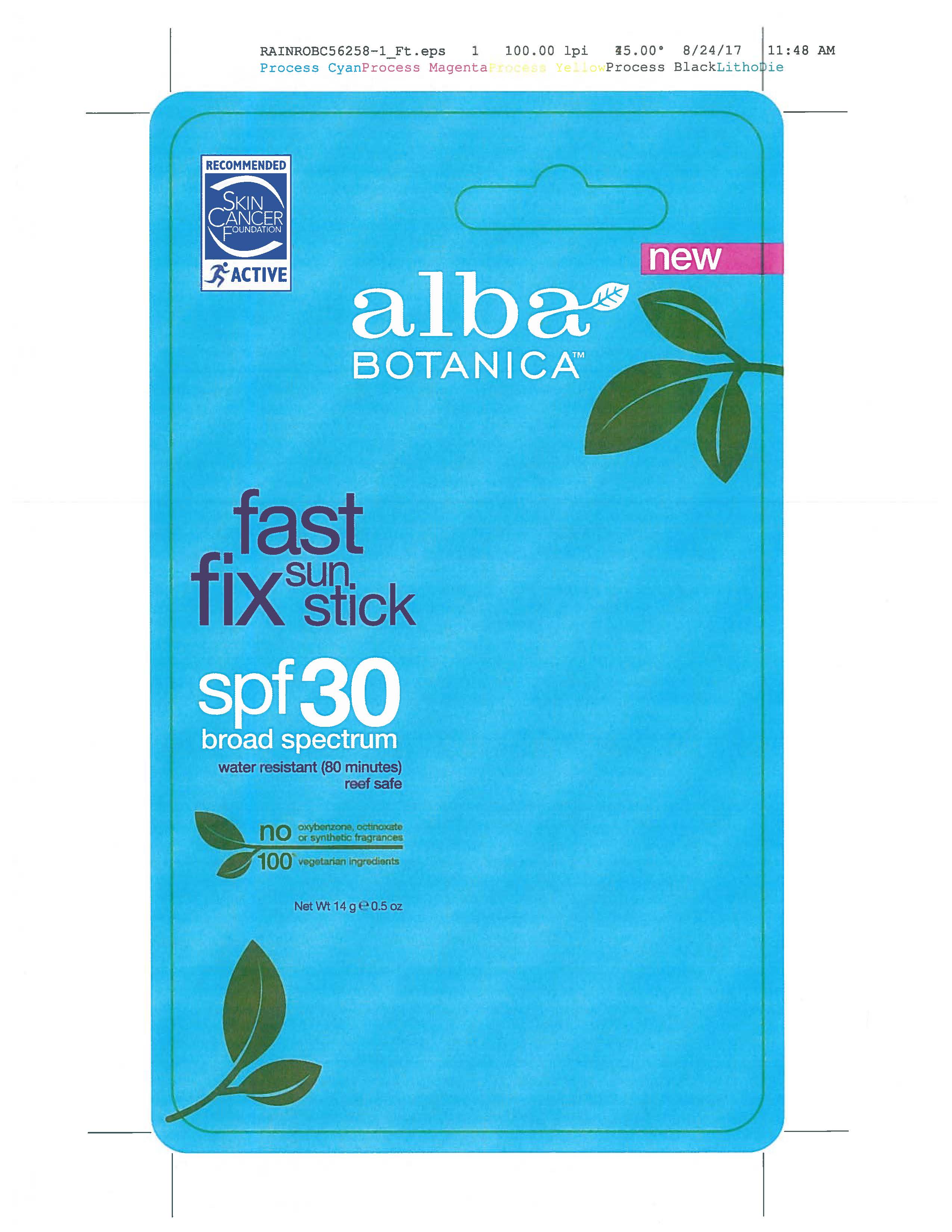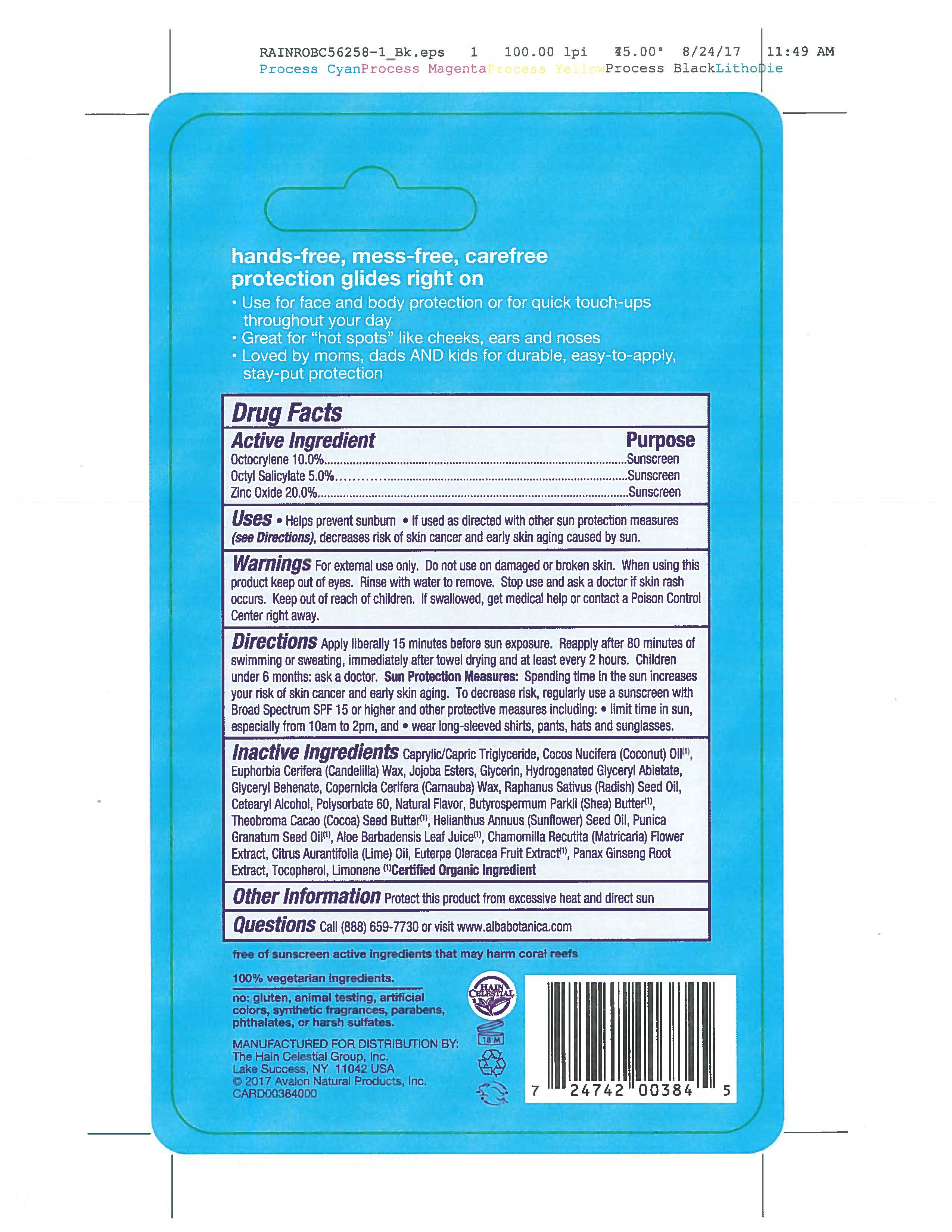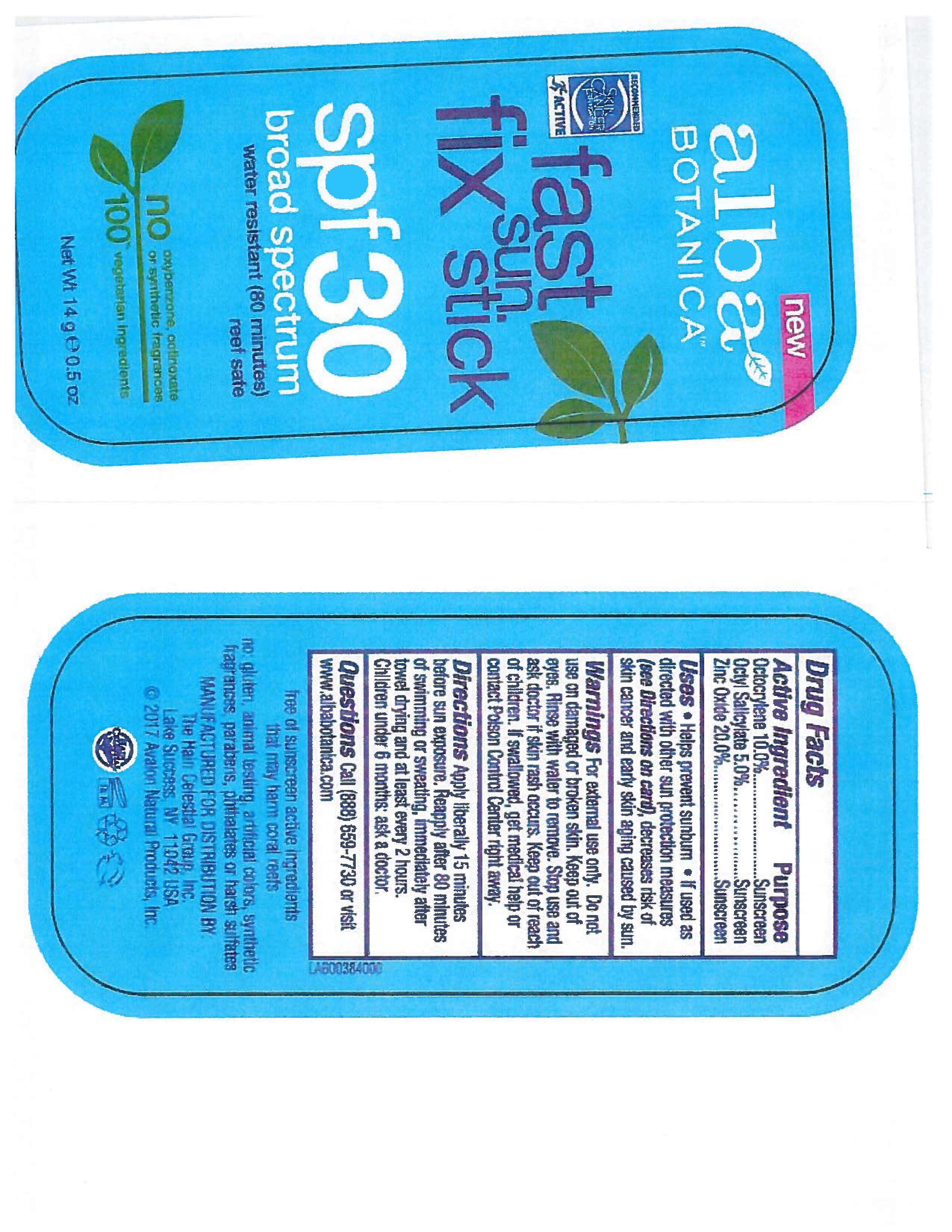 DRUG LABEL: AL0038400 Alba Botanica Fast Fix Sun SPF30
NDC: 61995-2384 | Form: STICK
Manufacturer: The Hain Celestial Group, Inc.
Category: otc | Type: HUMAN OTC DRUG LABEL
Date: 20241128

ACTIVE INGREDIENTS: ZINC OXIDE 20 g/100 g; OCTISALATE 5 g/100 g; OCTOCRYLENE 10 g/100 g
INACTIVE INGREDIENTS: TOCOPHEROL; ALOE VERA LEAF; GLYCERIN; SHEA BUTTER; CHAMOMILE; CETOSTEARYL ALCOHOL; POLYSORBATE 60; GLYCERYL MONOBEHENATE; CARNAUBA WAX; COCOA BUTTER; SUNFLOWER OIL; PUNICA GRANATUM SEED OIL; MEDIUM-CHAIN TRIGLYCERIDES; COCONUT OIL; CANDELILLA WAX; GLYCERYL ABIETATE; HYDROGENATED JOJOBA OIL, RANDOMIZED; RAPHANUS SATIVUS VAR. SATIVUS SEED

Alba Botanica Fast Fix Sun Stick SPF 30

Active Ingredient

Octyl Salicylate - 5.0%

Octocrylene - 10.0%

Zinc Ohide - 20.0%

DOSAGE AND ADMINISTRATION

Apply liberally 15 minutes before sun exposure. Reapply after 80 minutes of swimming or sweating, immediately after towel dryingt and at least every 2 hours. Children under 6 months: ask a doctor.

PURPOSE

Sunscreen

WARNINGS

For external use only. Do not use on damaged or broken skin. When using this product keep out of eyes. Rinse with water to remove. Stop use and ask a doctor if skin rash occurs.

Keep out of reach of children. If swallowed get medical help or contact Poison Center right away.

INACTIVE INGREDIENT

Caprylic/Capric Trigluceride, Cocos Nucifera (Cococnut) Oil (1), Euphorbia Cerifera (Candelilla) Wax, Jojoba Esters, Glycerin, Hydrogenated Glyceryl Abietate, Glyceryl Behenate, Copernicia Cerifera (Carnauba) Wax, Cetearyl Alcohol, Raphanus Sativus (Radish) Seed Oil, Aloe Barbadensis Leaf Juice(1), Chamomilla Recutita (Matricaria) Flower Extract (1), Butyrospermum Parkii (Shea) Butter (1), Polysorbate 60, Tocopheryol, Theobroma Cacao (Cocoa) Seed Butter (1), Punica Granatum Seed Oil (1), Helianthus Annuus (Sunflower)Seed Oil, Natural Flavor, Citrus Aurantifolia (Lime) Oil,Euterpe Oleracea Fruit Extract (1), Panax Ginseng Root Extract.

(1) Certified Organicf Ingredient

INDICATIONS AND USAGE

Helps prevents sunburns. If uses as directed with other sun protection measures, decreases risk of skin cancer and early skin aging caused by sun exposure. Skin Protection Measures: Spending time in the sun increases your risk of skin cancer and early skin aging. To decrease risk, regularly use sunscreen with Broad Spectrum SPF 15 or higher and other protective measures including: limit time in sun, especially from10am to 2pm, and wear long sleeved shirts, pants, hats and sunglases.